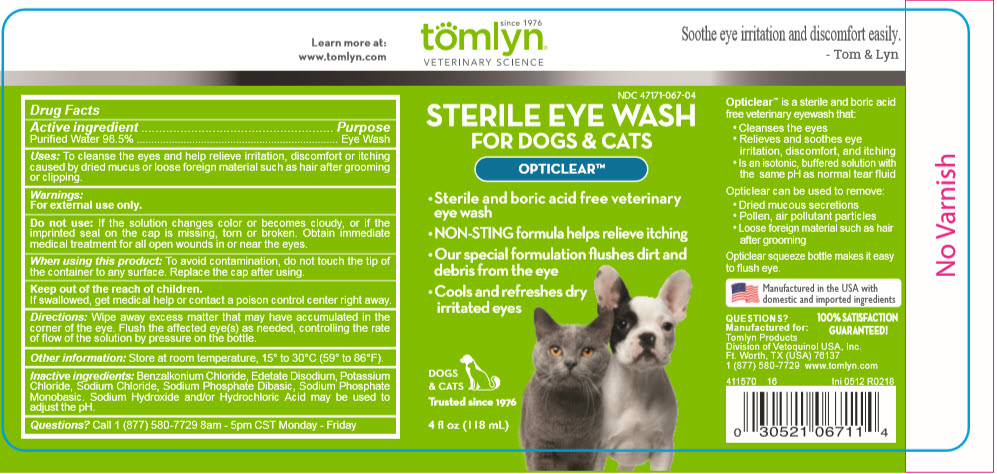 DRUG LABEL: Opticlear
NDC: 47171-067 | Form: LIQUID
Manufacturer: Tomlyn Products, a Divison of Vetoquinol USA, Inc.
Category: animal | Type: OTC ANIMAL DRUG LABEL
Date: 20201211

ACTIVE INGREDIENTS: Water 116.35 mL/118 mL
INACTIVE INGREDIENTS: BENZALKONIUM CHLORIDE; EDETATE DISODIUM; POTASSIUM CHLORIDE; SODIUM CHLORIDE; SODIUM PHOSPHATE, DIBASIC, UNSPECIFIED FORM; SODIUM PHOSPHATE, MONOBASIC, UNSPECIFIED FORM; SODIUM HYDROXIDE; HYDROCHLORIC ACID

OPTICLEAR™

Learn more at:
www.tomlyn.com

since 1976
tomlyn®
VETERINARY SCIENCE

Soothe eye irritation and discomfort easily.
- Tom & Lyn

Drug Facts

Active ingredient | Purpose
Purified Water 98.5% | Eye Wash

VETERINARY INDICATIONS

Uses: To cleanse the eyes and help relieve irritation, discomfort or itching caused by dried mucus or loose foreign material such as hair after grooming or clipping.

Warnings:

For external use only.

Do not use: If the solution changes color or becomes cloudy, or if the imprinted seal on the cap is missing, torn or broken. Obtain immediate medical treatment for all open wounds in or near the eyes.

When using this product: To avoid contamination, do not touch the tip of the container to any surface. Replace the cap after using.

Keep out of the reach of children.

If swallowed, get medical help or contact a poison control center right away.

DOSAGE AND ADMINISTRATION

Directions: Wipe away excess matter that may have accumulated in the corner of the eye. Flush the affected eye(s) as needed, controlling the rate of flow of the solution by pressure on the bottle.

Other information: Store at room temperature, 15° to 30°C (59° to 86°F).

INACTIVE INGREDIENT

Inactive ingredients: Benzalkonium Chloride, Edetate Disodium, Potassium Chloride, Sodium Chloride, Sodium Phosphate Dibasic, Sodium Phosphate Monobasic. Sodium Hydroxide and/or Hydrochloric Acid may be used to adjust the pH.

Questions? Call 1 (877) 580-7729 8am - 5pm CST Monday - Friday

Opticlear™ is a sterile and boric acid free veterinary eyewash that:

- Cleanses the eyes
- Relieves and soothes eye irritation, discomfort, and itching
- Is an isotonic, buffered solution with the same pH as normal tear fluid

Opticlear can be used to remove:

- Dried mucous secretions
- Pollen, air pollutant particles
- Loose foreign material such as hair after grooming

Opticlear squeeze bottle makes it easy to flush eye.

Manufactured in the USA with domestic and imported ingredients

QUESTIONS?

Manufactured for:
Tomlyn Products
Division of Vetoquinol USA, Inc.
Ft. Worth, TX (USA) 76137
1 (877) 580-7729 www.tomlyn.com

411570
16
Ini 0512 R0218

100% SATISFACTION GUARANTEED!

PRINCIPAL DISPLAY PANEL - 118 mL Bottle Label

NDC 47171-067-04

STERILE EYE WASH
FOR DOGS & CATS

OPTICLEAR™

- Sterile and boric acid free veterinary
  eye wash
- NON-STING formula helps relieve itching
- Our special formulation flushes dirt and
  debris from the eye
- Cools and refreshes dry
  irritated eyes

DOGS
& CATS

Trusted since 1976

4 fl oz (118 mL)